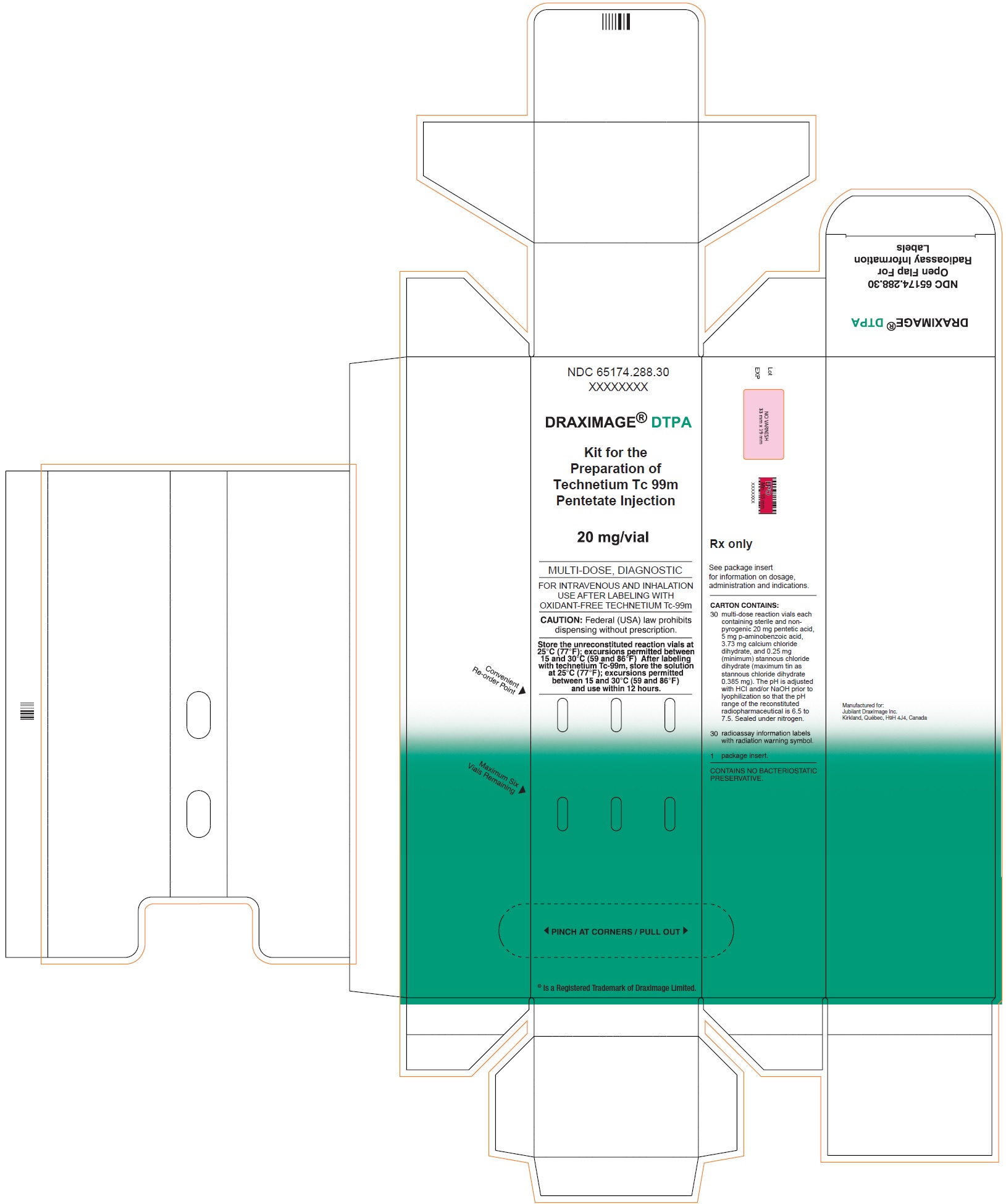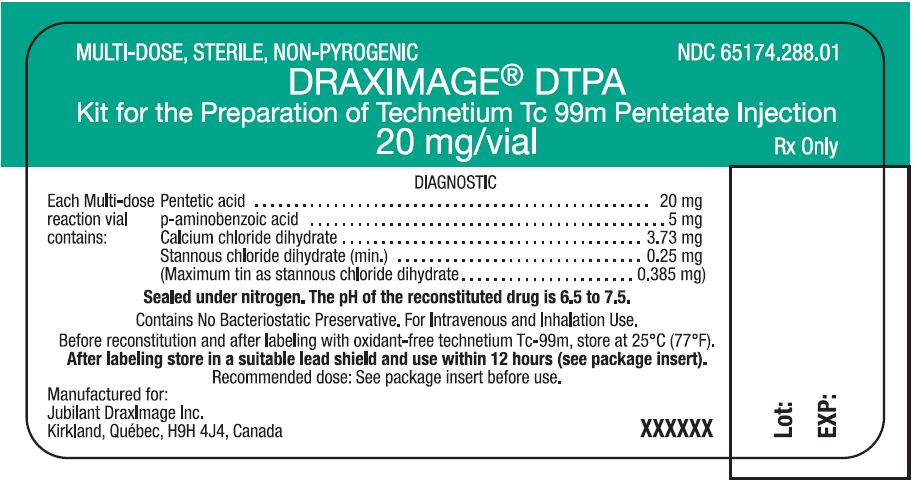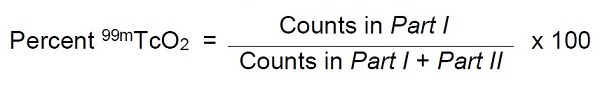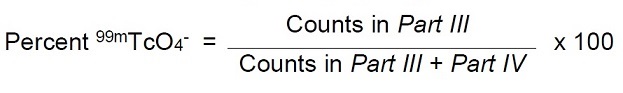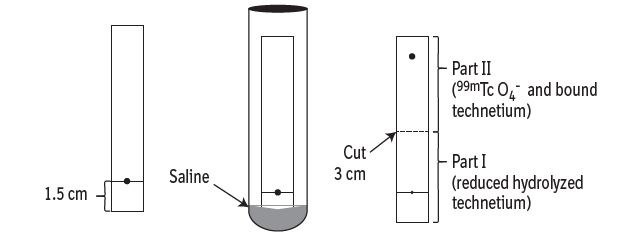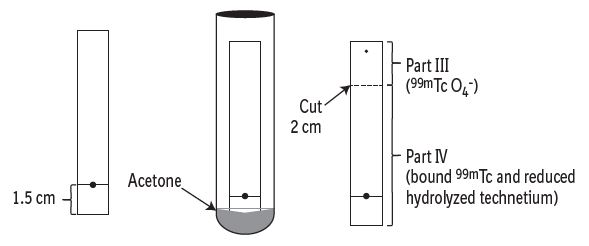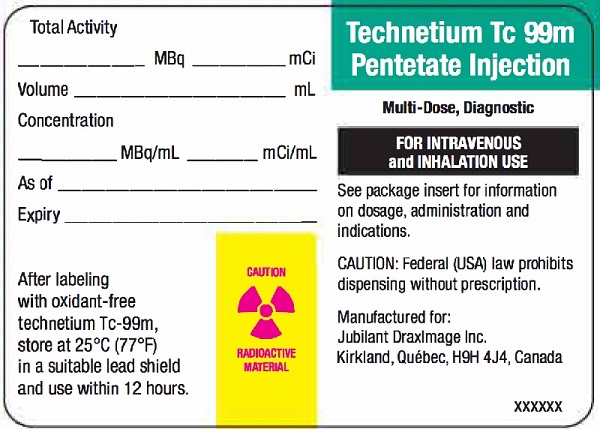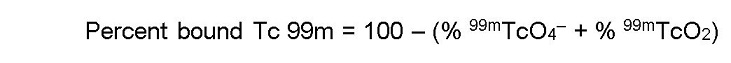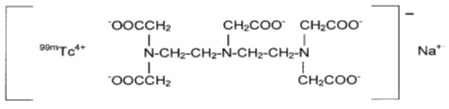 DRUG LABEL: DRAXIMAGE DTPA
NDC: 65174-288 | Form: INJECTION, POWDER, LYOPHILIZED, FOR SOLUTION
Manufacturer: Jubilant DraxImage Inc., dba Jubilant Radiopharma
Category: prescription | Type: HUMAN PRESCRIPTION DRUG LABEL
Date: 20230508

ACTIVE INGREDIENTS: Pentetic Acid 20 mg/1 1
INACTIVE INGREDIENTS: Aminobenzoic Acid 5 mg/1 1; Calcium Chloride 3.73 mg/1 1; Stannous Chloride 0.25 mg/1 1

HIGHLIGHTS OF PRESCRIBING INFORMATION

These highlights do not include all the information needed to use DRAXIMAGE® DTPA safely and effectively. See full prescribing information for DRAXIMAGE® DTPA.
DRAXIMAGE® DTPA (kit for the preparation of Technetium Tc 99m pentetate injection), for intravenous and inhalation use.
Initial U.S. Approval: 1974

RECENT MAJOR CHANGES

Dosage and Administration,
Determination of Radiochemical Purity (2.5) | 5/2022

1 INDICATIONS AND USAGE

DRAXIMAGE® DTPA is a kit for the preparation of Technetium Tc 99m pentetate injection. Technetium Tc 99m pentetate is a radioactive diagnostic agent indicated for:

- Brain imaging in adults (1.1).
- Renal visualization, assessment of renal perfusion, and estimation of glomerular filtration rate in adult and pediatric patients (1.2).
- Lung ventilation imaging and evaluation of pulmonary embolism when paired with perfusion imaging in adult and pediatric patients (1.3).

2 DOSAGE AND ADMINISTRATION

- During preparation and handling, use water proof gloves and effective shielding, to minimize radiation exposure (2.1, 5.3).
- See the Full Prescribing Information for detailed information regarding recommended Dosage and Image Acquisition Instructions (2.2) and Instructions for Drug Preparation (2.4).
- Do not administer more than one dose (2.2).

3 DOSAGE FORMS AND STRENGTHS

Kit for the preparation of Technetium Tc 99m pentetate injection: 10 mL multiple dose vials containing up to 9250 MBq / mL (250 mCi / mL) at time of preparation (reconstitution) (3).

4 CONTRAINDICATIONS

Hypersensitivity to the active ingredient or any component of this product (4).

5 WARNINGS AND PRECAUTIONS

- Hypersensitivity reactions: Hypersensitivity reactions, including anaphylaxis, have been reported during post-approval diagnostic use of Technetium Tc 99m pentetate injection. Monitor all patients for hypersensitivity reactions (5.1).
- Image interpretation risks in lung ventilation studies: If proximal airway deposition is observed, consider additional diagnostic options (5.2).
- Radiation exposure risk: Technetium Tc 99m pentetate contributes to a patient’s overall long-term radiation exposure (2.1, 2.3, 5.3).
- Bronchospasm in lung ventilation studies: Inhalation of Technetium Tc 99m pentetate solution may result in acute bronchoconstriction, especially in patients with heightened bronchoreactivity (5.4).

6 ADVERSE REACTIONS

Most common adverse reactions reported with Technetium Tc 99m pentetate injection include allergic reactions, rash, itching (6).

To report SUSPECTED ADVERSE REACTIONS, contact Jubilant DraxImage Inc. at 1-888-633-5343 or FDA at 1-800-FDA-1088 or www.fda.gov/medwatch.

FULL PRESCRIBING INFORMATION

1 INDICATIONS AND USAGE

DRAXIMAGE® DTPA, after radiolabeling with Technetium Tc 99m, is indicated for

1.1 Brain Imaging

Brain imaging in adults by intravenous administration.

1.2 Renal Scintigraphy

Renal visualization, assessment of renal perfusion, and estimation of glomerular filtration rate in adult and pediatric patients by intravenous administration.

1.3 Lung Ventilation Imaging

Lung ventilation imaging and evaluation of pulmonary embolism when paired with perfusion imaging in adult and pediatric patients when administered by nebulizer for inhalation.

2 DOSAGE AND ADMINISTRATION

2.1 Radiation Safety – Drug Handling

Tc 99m labeled DRAXIMAGE® DTPA injection is a radioactive drug and should be handled with appropriate safety measures to minimize radiation exposure to the patient and healthcare worker. During preparation and handling, use water proof gloves and effective shielding, including syringe shields [see Warnings and Precautions (5.3)].

2.2 Recommended Dosage and Image Acquisition Instructions

- The recommended dose ranges for intravenous or inhalation administration of DRAXIMAGE® DTPA, after reconstitution, are presented in Table 1 through Table 3.
- Do not administer more than one dose.

Table 1 Tc 99m Labeled DRAXIMAGE® DTPA Injection – Intravenous Administration, Adults
Indication | Route of Administration | Dose | Image Acquisition
Brain Imaging | Intravenous Injection | 370 MBq to 740 MBq (10 mCi to 20 mCi) | Immediate dynamic imaging. Obtain at least one blood-pool image in same position as flow. Delayed images can be obtained 1 hour later.
Renal Visualization and Perfusion Assessment | Intravenous Injection | 370 MBq to 740 MBq (10 mCi to 20 mCi) | Immediate dynamic imaging. Static imaging 1 to 30 minutes after injection.
Renal Visualization with Estimation of Glomerular Filtration Rate | Intravenous Injection | 111 MBq to 185 MBq (3 mCi to 5 mCi) | Immediate dynamic imaging. Static imaging 1 to 30 minutes after injection.
Estimation of Glomerular Filtration Rate (with no renal imaging) | Intravenous Injection | 7.4 MBq to 18.5 MBq (0.2 mCi to 0.5 mCi) | Blood sampling only is performed.

Table 2 Tc 99m Labeled DRAXIMAGE® DTPA Injection – Intravenous Administration, Pediatric Patients
Indication | Route of Administration | Dose | Image Acquisition
Renal Visualization and Perfusion Assessment | Intravenous Injection | 3.7 MBq/kg to 7.4 MBq/kg (0.1 mCi/kg to 0.2 mCi/kg) Minimum 37 MBq (1 mCi) Maximum 185 MBq (5 mCi) | Immediate dynamic imaging. Static imaging 1 to 30 minutes after injection.
Estimation of Glomerular Filtration Rate (with no renal imaging) | Intravenous Injection | 7.4 MBq to 18.5 MBq (0.2 mCi to 0.5 mCi) | Blood sampling only is performed.

Table 3 Tc 99m Labeled DRAXIMAGE® DTPA – Aerosol Inhalation Administration
Indication | Route of Administration | Dose | Image Acquisition
Lung Ventilation Adults | Aerosol Inhalation | 925 MBq to 1850 MBq (25 mCi to 50 mCi) in the nebulizer to achieve a lung dose of approximately 18.5 MBq to 37 MBq (0.5 mCi to 1.0 mCi) | For lung imaging performed prior to perfusion imaging, the target administered dose to the lungs is achieved after 3 to 5 minutes of inhalation or at an imaging count rate of 50,000 to 100,000 per minute*.
Lung Ventilation Pediatric Patients | Aerosol Inhalation | 925 MBq (25 mCi) in the nebulizer to achieve a lung dose of approximately 18.5 MBq (0.5 mCi) | For lung imaging performed prior to perfusion imaging, the target administered dose to the lungs is achieved at an imaging count rate of approximately 10,000 to 50,000 per minute*.
* For lung imaging performed after perfusion imaging, target count rate should be approximately three times that of perfusion count rate.

2.3 Administration Instructions

- Use aseptic technique for all drug preparation and handling.
- Visually inspect the Tc 99m labeled DRAXIMAGE® DTPA injection after reconstitution for particulate matter prior to administration. Do not use or administer if there is evidence of foreign matter or the solution is not clear.
- Measure the patient dose by a radioactivity calibration system immediately prior to administration.

Intravenous Use

- Instruct the patient to increase fluid intake and to void frequently for the next 4 to 6 hours after Tc 99m labeled DRAXIMAGE® DTPA administration by injection to minimize the radiation dose to the bladder.

Inhalation Use

- Use the selected nebulizer in accordance with the manufacturer’s instructions.
- Instruct the patient to rinse their mouth and expectorate after Tc 99m labeled DRAXIMAGE® DTPA administration by inhalation to minimize the radiation dose to the mouth and esophagus.

2.4 Instructions for Drug Preparation

- The prepared solution can either be administered via intravenous injection or aerosolized by nebulizer for inhalation use.
- Before reconstitution, inspect the integrity of the vial.
- Add 2 to 10 mL [maximum amount 18.5 gigabecquerels (500 mCi)] of sodium pertechnetate Tc 99m injection USP to the reaction vial. The volume of pertechnetate added should be balanced by the removal of the same volume of air. Cover the vial shield and invert to mix the contents.
- Assay the preparation in a calibrator, record the radio assay information on the label with radiation warning symbol, and affix it to the reaction vial.
- After reconstitution, store the solution at 25 °C (77 °F) in a lead shield and discard after 12 hours; excursions permitted between 15 °C and 30 °C (59 °F and 86°F).
- Allow the preparation to stand for 15 minutes before determining the radiochemical purity of Tc 99m labeled DRAXIMAGE® DTPA injection.
- After reconstitution, do not vent the vial.

2.5 Determination of Radiochemical Purity

Obtain the following:

- Two ITLC-SG (1 x 10 cm)
- 0.9% Sodium Chloride Injection USP (for determination of reduced hydrolyzed technetium)
- Acetone (for determination of free pertechnetate)
- Two glass test tubes (18 mm x 150 mm) with stoppers

Step 1:

- System A: Add 1 mL of 0.9% Sodium Chloride Injection USP in an 18 mm x 150 mm test tube. Place the stopper and allow the atmosphere in the tube to equilibrate for 1 minute.
- System B: Repeat with Acetone in a separate test tube.

Step 2:

- Mark each chromatographic strip with a pencil mark 1.5 cm (see Figure 1 and Figure 2) from one end of the strip (mark as origin).
- Place one drop (approximately 0.01 to 0.02 mL) of the Technetium Tc 99m pentetate injection at the origin.
- For System A (saline), do not allow the strip to dry.
- For System B (acetone), dry the strip using a gentle stream of nitrogen gas.

Step 3:

- Place each strip with the origin end towards the bottom of the previously equilibrated test tube to develop (the origin must be above the surface of the solvent).
- Place stopper in the test tube and keep upright.

Step 4:

- When the solvent front has reached the top of the strip, remove the strip with forceps and allow it to dry.

Step 5:
System A – Determination of reduced hydrolyzed technetium:

- In System A (saline), reduced hydrolyzed technetium (99m TcO2) stays at the origin (Rf 0 to 0.1), while the bound technetium and free pertechnetate (99m TcO4^–) migrates to the solvent front (Rf 0.85 to 1.0).
- Cut the dried strip 3 cm from the origin.
- The short piece is marked as Part I and the long piece is marked as Part II.
- Count the pieces in a counter and determine the percentage of reduced hydrolyzed technetium according to the following formula:

Figure 1 System A Diagram

System B – Determination of free pertechnetate:

- In System B (acetone), the bound technetium (99mTc) and reduced hydrolyzed technetium (99m TcO2) stay at the origin (Rf 0 to 0.1), while free pertechnetate (99m TcO4^–) migrates to the solvent front (Rf 0.85 to 1.0).
- Cut the dried strip 2 cm from the solvent front end.
- The short piece is marked Part III and the long piece is marked Part IV.
- Count the pieces in a counter and determine the percentage of free pertechnetate according to the following formula:

Figure 2 System B Diagram

Step 6:

- Determine the radiochemical purity according to the following formula:

- Use Technetium Tc 99m pentetate injection only if the radiochemical purity is 90% or greater.

2.6 Radiation Dosimetry

The estimated radiation absorbed dose to various organs from an intravenous injection of Tc 99m pentetate in patients with normal and abnormal renal function is shown respectively in Table 4 and Table 5.

Table 4 Estimated Radiation Absorbed Dose for Technetium Tc 99m Pentetate Injection in Patients With Normal Renal Function Following Intravenous Injection
Absorbed Dose Per Unit Activity Administered (microGy/MBq)
Organ |  | Adult | 15 Years | 10 Years | 5 Years | 1 Year
Adrenals |  | 1.4 | 1.8 | 2.7 | 4.0 | 7.2
Bone surfaces |  | 2.4 | 2.9 | 4.3 | 6.1 | 10
Brain |  | 0.86 | 1.1 | 1.7 | 2.8 | 4.9
Breast |  | 0.72 | 0.92 | 1.3 | 2.2 | 4.1
Gallbladder wall |  | 1.5 | 2.1 | 3.8 | 5.0 | 6.1
Gastrointestinal tract
 | Esophagus | 1.0 | 1.3 | 1.9 | 3.0 | 5.4
 | Stomach wall | 1.3 | 1.7 | 2.8 | 4.0 | 6.8
 | Small intestine wall | 2.5 | 3.1 | 4.9 | 7.0 | 10
 | Colon wall | 3.1 | 3.9 | 6.0 | 8.1 | 11
 | Upper large intestine wall | 2.1 | 2.8 | 4.3 | 6.5 | 9.2
 | Lower large intestine wall | 4.3 | 5.4 | 8.2 | 10 | 13
Heart wall |  | 1.2 | 1.5 | 2.2 | 3.3 | 5.9
Kidneys |  | 4.4 | 5.3 | 7.5 | 11 | 18
Liver |  | 1.2 | 1.6 | 2.5 | 3.8 | 6.4
Lungs |  | 1.0 | 1.3 | 2.0 | 3.0 | 5.5
Muscles |  | 1.6 | 2.0 | 3.0 | 4.3 | 6.8
Ovaries |  | 4.2 | 5.3 | 7.7 | 10 | 13
Pancreas |  | 1.4 | 1.8 | 2.8 | 4.3 | 7.4
Red marrow |  | 1.5 | 1.8 | 2.7 | 3.7 | 5.7
Skin |  | 0.87 | 1.0 | 1.7 | 2.6 | 4.4
Spleen |  | 1.3 | 1.6 | 2.6 | 3.9 | 6.8
Testes |  | 2.9 | 4.0 | 6.8 | 9.4 | 13
Thymus |  | 1.0 | 1.3 | 1.9 | 3.0 | 5.4
Thyroid |  | 1.0 | 1.3 | 2.1 | 3.3 | 6.0
Urinary bladder wall |  | 62 | 78 | 110 | 150 | 170
Uterus |  | 7.9 | 9.6 | 15 | 18 | 22
Remaining organs |  | 1.7 | 2.1 | 3.0 | 4.2 | 6.6
Effective dose per unit activity (microSv/MBq) |  | 4.9 | 6.3 | 9.4 | 12 | 16

Table 5 Estimated Radiation Absorbed Dose for Technetium Tc 99m Pentetate Injection in Patients With Abnormal Renal Function Following Intravenous Injection
Absorbed Dose Per Unit Activity Administered (microGy/MBq)
Organ |  | Adult | 15 Years | 10 Years | 5 Years | 1 Year
Adrenals |  | 4.1 | 5.1 | 7.6 | 11 | 21
Bone surfaces |  | 6.0 | 7.1 | 11 | 15 | 28
Brain |  | 2.8 | 3.5 | 5.7 | 9.1 | 16
Breast |  | 2.3 | 3.0 | 4.2 | 6.8 | 13
Gallbladder wall |  | 4.2 | 5.7 | 9.2 | 13 | 16
Gastrointestinal tract
 | Esophagus | 3.3 | 4.2 | 6.2 | 9.6 | 17
 | Stomach wall | 3.8 | 5.0 | 7.9 | 11 | 19
 | Small intestine wall | 4.5 | 5.6 | 8.5 | 13 | 22
 | Colon wall | 4.5 | 5.8 | 8.7 | 13 | 22
 | Upper large intestine wall | 4.3 | 5.6 | 8.1 | 13 | 21
 | Lower large intestine wall | 4.9 | 6.1 | 9.5 | 13 | 23
Heart wall |  | 3.7 | 4.7 | 7.0 | 10 | 18
Kidneys |  | 7.7 | 9.2 | 13 | 19 | 32
Liver |  | 3.7 | 4.6 | 7.1 | 11 | 19
Lungs |  | 3.3 | 4.2 | 6.2 | 9.5 | 17
Muscles |  | 3.2 | 4.0 | 6.1 | 9.1 | 17
Ovaries |  | 5.0 | 6.2 | 9.2 | 14 | 23
Pancreas |  | 4.3 | 5.3 | 8.0 | 12 | 21
Red marrow |  | 3.4 | 4.2 | 6.4 | 9.3 | 16
Skin |  | 2.2 | 2.6 | 4.2 | 6.7 | 12
Spleen |  | 3.8 | 4.7 | 7.3 | 11 | 19
Testes |  | 3.5 | 4.5 | 6.9 | 10 | 18
Thymus |  | 3.3 | 4.2 | 6.2 | 9.6 | 17
Thyroid |  | 3.4 | 4.2 | 6.7 | 11 | 19
Urinary bladder wall |  | 21 | 27 | 39 | 50 | 66
Uterus |  | 6.1 | 7.4 | 11 | 16 | 25
Remaining organs |  | 3.3 | 4.1 | 6.3 | 9.7 | 17
Effective dose per unit activity (microSv/MBq) |  | 4.6 | 5.8 | 8.7 | 13 | 21

The estimated radiation absorbed dose to various organs from the inhalation of Tc 99m Pentetate Injection is shown in Table 6.

Table 6 Estimated Radiation Absorbed Dose for Technetium Tc 99m Pentetate Injection Administered by Inhalation
Absorbed Dose Per Unit Activity Administered (microGy/MBq)
Organ |  | Adult | 15 Years | 10 Years | 5 Years | 1 Year
Adrenals |  | 2.1 | 2.9 | 4.4 | 6.7 | 12
Bone surfaces |  | 1.9 | 2.4 | 3.5 | 5.3 | 9.8
Breast |  | 1.9 | 1.9 | 3.3 | 4.8 | 7.8
Gastrointestinal tract
 | Stomach wall | 1.7 | 2.2 | 3.5 | 5.1 | 8.9
 | Small intestine wall | 2.1 | 2.6 | 4.1 | 6.3 | 11
 | Upper large intestine wall | 1.9 | 2.4 | 3.8 | 6.1 | 10
 | Lower large intestine wall | 3.2 | 4.2 | 6.3 | 8.8 | 15
Kidneys |  | 4.1 | 5.1 | 7.2 | 11 | 19
Liver |  | 1.9 | 2.5 | 3.7 | 5.5 | 9.7
Lungs |  | 17 | 26 | 36 | 54 | 100
Ovaries |  | 3.3 | 4.1 | 6.1 | 8.9 | 15
Pancreas |  | 2.1 | 2.6 | 4.0 | 6.1 | 11
Red marrow |  | 2.7 | 3.4 | 4.7 | 6.2 | 9.6
Spleen |  | 1.9 | 2.4 | 3.6 | 5.6 | 9.9
Testes |  | 2.1 | 3.1 | 5.2 | 7.9 | 15
Thyroid |  | 0.99 | 1.7 | 2.7 | 4.4 | 7.8
Urinary bladder wall |  | 47 | 58 | 84 | 120 | 230
Uterus |  | 5.9 | 7.2 | 11 | 16 | 27
Other tissue |  | 1.8 | 2.2 | 3.2 | 4.9 | 8.6
Effective dose per unit activity (microSv/MBq) |  | 5.9 | 8.0 | 11 | 17 | 31

3 DOSAGE FORMS AND STRENGTHS

Kit for the preparation of Technetium Tc 99m pentetate injection: multiple-dose 10 mL glass vial contains a non-radioactive (white) lyophilized powder with 20 mg of pentetic acid, 5 mg of p-aminobenzoic acid, 3.73 mg of calcium chloride dihydrate, and not less than 0.25 mg stannous chloride dihydrate and not more than 0.385 mg maximum tin expressed as stannous chloride dihydrate. The lyophilized product is sealed under an atmosphere of nitrogen.

Following reconstitution with the Technetium Tc 99m eluate, the radioactive solution produced is a clear solution not exceeding 9250 MBq/mL (250 mCi/mL) of Tc 99m.

4 CONTRAINDICATIONS

Hypersensitivity to the active ingredient or to any component of the product [see Warnings and Precautions (5.1)].

5 WARNINGS AND PRECAUTIONS

5.1 Hypersensitivity Reactions

Hypersensitivity reactions, including anaphylaxis, have been reported during post-approval diagnostic use of Technetium Tc 99m pentetate injection. Monitor all patients for hypersensitivity reactions and have access to cardiopulmonary resuscitation equipment and personnel.

5.2 Image Interpretation Risks in Lung Ventilation Studies

In patients with obstructive pulmonary disease there may be deposition of particles in the proximal airways influencing image quality and interfering with diagnostic interpretation, therefore to ensure diagnostic quality, careful use of the nebulizer to assure optimal particle delivery is essential. If interfering particle deposition occurs, consider additional diagnostic options.

5.3 Radiation Exposure Risk

Technetium Tc 99m contributes to a patient’s overall long-term cumulative radiation exposure. Long-term cumulative radiation exposure is associated with an increased risk of cancer. Ensure safe handling and preparation procedures to protect patients and health care workers from unintentional radiation exposure. Use the lowest dose of Technetium Tc 99m pentetate necessary for imaging. Encourage patients to drink fluids and void as frequently as possible after intravenous administration [see Dosage and Administration (2.1, 2.3)].

Radiation risks associated with the use of Technetium Tc 99m pentetate are greater in pediatric patients than in adults due to greater radiosensitivity and longer life expectancy.

5.4 Bronchospasm in Lung Ventilation Studies

As with other inhaled medications, inhalation of Technetium Tc 99m pentetate solution may result in acute bronchoconstriction, especially in patients with heightened bronchoreactivity, such as patients with asthma or other lung or allergic disorders. Monitor all patients for bronchoconstriction.

6 ADVERSE REACTIONS

The following adverse reactions have been identified post-approval. Because these reactions are voluntarily reported from a population of uncertain size, it is not always possible to reliably estimate their exact frequency or establish a causal relationship to Technetium Tc 99m pentetate exposure.

Adverse reactions are presented in decreasing order of reported frequency:

- Immune system disorders: allergic reaction, anaphylactic reaction, angioedema.
- Skin and subcutaneous tissue disorders: rash, itching, hives, erythema.
- Respiratory, thoracic and mediastinal disorders: throat irritation, wheezing.
- Vascular disorders: hypotension, hypertension.
- Nervous system disorders: headache, fainting, dizziness.
- General disorders and administration site conditions: chills.
- Gastrointestinal disorders: nausea, vomiting.
- Cardiac disorders: cyanosis, tachycardia.

8 USE IN SPECIFIC POPULATIONS

8.1 Pregnancy

Risk Summary

Limited available data with Technetium Tc 99m pentetate use in pregnant women are insufficient to inform a drug associated risk for major birth defects and miscarriage. Technetium Tc 99m pentetate is transferred across the placenta (see Data). No animal reproductive studies have been conducted with Technetium Tc 99m pentetate. All radiopharmaceuticals have the potential to cause fetal harm depending on the fetal stage of development and the magnitude of the radiation dose. If considering Technetium Tc 99m pentetate administration to a pregnant woman, inform the patient about the potential for adverse pregnancy outcomes based on the radiation dose from Technetium Tc 99m pentetate and the gestational timing of exposure.

The estimated background risk of major birth defects and miscarriage for the indicated population is unknown. In the U.S., general population, the estimated background risk of major birth defects and miscarriage in clinically recognized pregnancies are 2% to 4% and 15% to 20%, respectively.

Data

Human Data
Limited published literature describes Technetium Tc 99m pentetate crossing the placental barrier. No adverse fetal effects or radiation-related risks have been identified for diagnostic procedures involving less than 50 mGy, which represents less than 10 mGy fetal doses.

8.2 Lactation

Risk Summary

There are limited data available in scientific literature on the presence of Technetium Tc 99m pentetate in human milk. There are no data available on the effects of Technetium Tc 99m pentetate on the breastfed infant or the effects on milk production. Based on the United States Nuclear Regulatory Commission guidelines for breast feeding interruption after exposure to radiopharmaceuticals, breastfeeding interruption is not recommended for Technetium 99m pentetate at levels less than 1000 MBq (30 mCi). The developmental and health benefits of breastfeeding should be considered along with the mother’s clinical need for Technetium Tc 99m pentetate, any potential adverse effects on the breastfed child from Technetium Tc 99m pentetate or from the underlying maternal condition.

8.4 Pediatric Use

Technetium Tc 99m pentetate is indicated for lung ventilation and evaluation of pulmonary embolism when paired with perfusion imaging and for renal visualization, assessment of renal perfusion, and estimation of glomerular filtration rate in pediatric patients ages birth to less than 17 years of age. Pediatric use is supported by evidence from controlled studies in adults and dosing and safety are based on clinical experience.

The radiation risk of Technetium Tc 99m pentetate is greater in pediatric patients than adults [See Warnings and Precautions, (5.3)].

8.5 Geriatric Use

No formal studies of Technetium Tc 99m pentetate in the elderly were performed to determine whether they respond differently from younger subjects. Other reported clinical experience has not identified differences in responses between the elderly and younger patients. In general, dose selection for an elderly patient should be cautious, usually starting at the low end of the dosing range, reflecting the greater frequency of decreased hepatic, renal, or cardiac function, and of concomitant disease or other drug therapy.

11 DESCRIPTION

11.1 Chemical Characteristics

DRAXIMAGE® DTPA is a kit for the preparation of Technetium Tc 99m pentetate injection, a radioactive diagnostic agent, for intravenous or inhalation use. Each multiple-dose 10 mL glass vial contains a sterile, non-pyrogenic, non-radioactive lyophilized powder of 20 mg of pentetic acid, 5 mg of p-aminobenzoic acid, 3.73 mg of calcium chloride dihydrate, and not less than 0.25 mg stannous chloride dihydrate and not more than 0.385 mg maximum tin expressed as stannous chloride dihydrate. The lyophilized product is sealed under an atmosphere of nitrogen. No bacteriostatic preservative is present. Its chemical name is:

Technetate (1-)99mTc,[N,N-bis[2-[bis(carboxymethyl)amino]ethyl]-glycinato(5-)]-, sodium. The structure of the technetium labeled form is:

The pH is adjusted with HCl and/or NaOH prior to lyophilization so that the pH range of the reconstituted radiopharmaceutical is 6.5 to 7.5.

11.2 Physical Characteristics

Technetium Tc 99m decays by isomeric transition with a physical half-life of 6 hours. The principal photon that is useful for detection and imaging studies is listed in Table 7.

Table 7 Principal Radiation Emission Data
Radiation | Mean % per Disintegration | Mean Energy (keV)
Gamma-2 | 88.5 | 140.5

The air-kerma-rate (exposure-rate) constant for Technetium Tc 99m is 5.23 m^2·pGy·(MBq)^−^1·s^−^1 [0.795 cm^2·R·(mCi)^−^1·h^−^1]. A range of values for the relative radiation attenuation by the various thicknesses of lead is shown in Table 8. For example, the use of a 3 mm thickness of lead will attenuate the radiation emitted by a factor of about 1,000.

Table 8 Radiation Attenuation by Lead Shielding
Shield Thickness (Pb) cm | Coefficient of Attenuation
0.25 | 0.5
1 | 10^-1
2 | 10^-2
3 | 10^-3
4 | 10^-4

To correct for physical decay of this radionuclide, the fractions that remain at selected intervals after the time of calibration are shown in Table 9.

Table 9 Physical Decay Chart of Technetium 99mTc, Half Life: 6 Hours
Hours | Fraction Remaining | Hours | Fraction Remaining
0* | 1.000 | 5 | 0.562
1 | 0.891 | 6 | 0.501
2 | 0.794 | 8 | 0.398
3 | 0.708 | 10 | 0.316
4 | 0.631 | 12 | 0.251
*Calibration Time

12 CLINICAL PHARMACOLOGY

12.1 Mechanism of Action

Intravenous Administration

Following intravenous administration for brain and renal imaging, Technetium Tc 99m pentetate is distributed in the vascular compartment. It is cleared by the kidneys, which results in the ability to image the kidney.

Aerosolized Inhalation Administration

Following inhalation of the aerosol, Technetium Tc 99m pentetate deposits on the epithelium of ventilated alveoli.

12.2 Pharmacodynamics

Brain Imaging

Technetium Tc 99m pentetate with intravenous administration tends to accumulate in intra-cranial lesions with excessive neovascularity or an altered blood brain barrier. Technetium Tc 99m pentetate accumulation in the brain is prevented by an intact blood brain barrier. It does not accumulate in the choroid plexus.

Renal Scintigraphy

The first few minutes after intravenous administration, Technetium Tc 99m pentetate is present in the vascular compartment within the renal system.

Lung Ventilation Imaging

In patients with normal lungs, the deposition of Technetium Tc 99m pentetate is homogeneous throughout the lungs. In patients with airway disease, the deposition patterns become inhomogeneous with irregular deposition of Technetium Tc 99m pentetate in the airways and alveolar regions of the lung.

12.3 Pharmacokinetics

After an intravenous administration, the pharmacokinetics of Technetium Tc 99m pentetate were studied by monitoring radioactivity in serial venous blood samples for 7 hours post-administration. The mean plasma clearance rate was 6.8 (L/h) and the mean plasma elimination half-life (t½) was 2.1 hours. The mean volume of distribution at steady state conditions calculated with clearance and mean residence time was 17 L. This relatively low volume of distribution after intravenous administration suggests that Technetium Tc 99m pentetate distributes to the extracellular fluid only. The rate of elimination of Technetium Tc 99m pentetate from the systemic circulation appears to be constant over an approximately 20-fold intravenous dose range.

Absorption

Following inhalation Technetium Tc 99m pentetate was absorbed (Tmax < 2 hours after inhalation) and distributed across the lung epithelium (bioavailability approximately 70%) and into the systemic circulation.

Distribution

Following intravenous administration, Technetium Tc 99m pentetate is distributed throughout the extracellular fluid space and is cleared from the body by the kidney.

The steady-state volume of distribution (Vss) was 17 L following an intravenous administration. Technetium Tc 99m pentetate distribution appears to be limited to the extravascular compartment.

A variable percentage of the Technetium Tc 99m pentetate binds to the serum proteins; this ranges from 3.7% following a single injection to approximately 10% if the material is continuously infused. Although the chelate gives useful information on the glomerular filtration rate, the variable percent which is protein bound leads to a measured renal clearance rate which is lower than that determined by inulin clearance.

Elimination

Metabolism

Technetium Tc 99m pentetate is not metabolized.

Excretion

After either intravenous administration or inhalation, excretion is by glomerular filtration. The mean fraction of intravenously administered Technetium Tc 99m pentetate excreted in urine over 24 hours was 102%.

16 HOW SUPPLIED/STORAGE AND HANDLING

16.1 How Supplied

DRAXIMAGE® DTPA is supplied as multiple dose kits consisting of 10 mL reaction vials containing a white, lyophilized powder with 20 mg of pentetic acid, 5 mg of p-aminobenzoic acid, 3.73 mg of calcium chloride dihydrate, and not less than 0.25 mg stannous chloride dihydrate and not more than 0.385 mg tin expressed as stannous chloride dihydrate.

The radionuclide is not part of the kit. Before reconstitution and radiolabeling with sodium pertechnetate Tc 99m injection USP, the contents of the kit are not radioactive.

The kits are supplied in the following formats:

Carton containing 30 (thirty) kits NDC 65174.288.30

16.2 Storage and Handling

Store the unreconstituted reaction vials at 25 °C (77 °F); excursions permitted between 15 °C and 30 °C (59 °F and 86 °F).

This radiopharmaceutical is approved for use by persons under license by the Nuclear Regulatory Commission or the relevant regulatory authority of an Agreement State.

17 PATIENT COUNSELING INFORMATION

Administration Instructions

Intravenous Use

Advise patients to hydrate after administration of Tc 99m labeled DRAXIMAGE® DTPA injection and to void frequently to minimize radiation dose [see Dosage and Administration (2.3)].

Inhalation Use

To minimize the potential of mouth and esophageal activity of Tc 99m labeled DRAXIMAGE® DTPA, advise the patient to rinse their mouth with water and spit it out prior to imaging [see Dosage and Administration (2.3)].

Pregnancy

Advise pregnant women of the risk of fetal exposure to radiation if they undergo a radionuclide procedure [see Use in Specific Populations (8.1)].

® Registered Trademark of Jubilant DraxImage Inc.

Manufactured for:
Jubilant DraxImage Inc., Kirkland,
Quebec, Canada, H9H 4J4.
Revised: May 2023
Art Rev.: 1.3